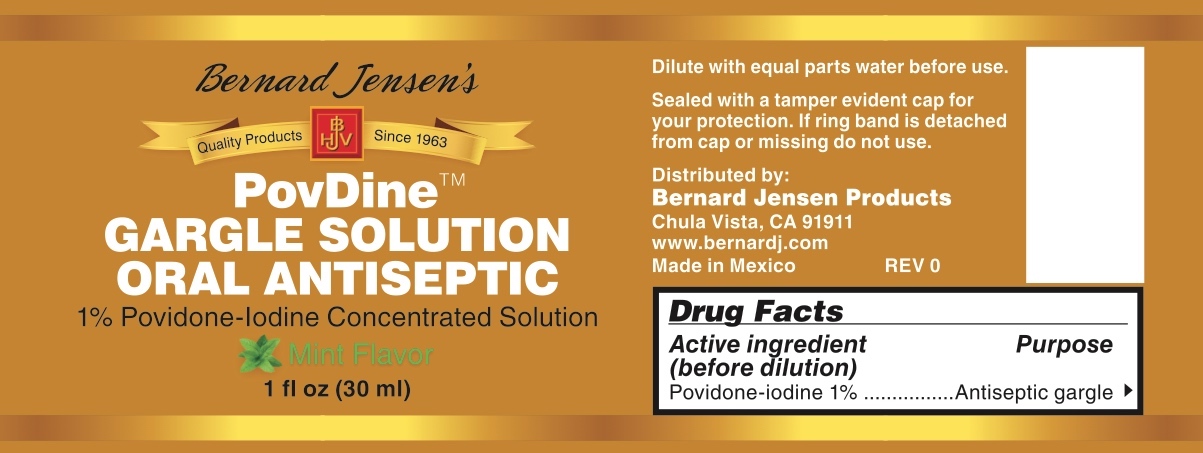 DRUG LABEL: Bernard Jensens PovDine
NDC: 79994-001 | Form: SOLUTION
Manufacturer: Great North, LLC, dba Bernard Jensen Products
Category: otc | Type: HUMAN OTC DRUG LABEL
Date: 20210112

ACTIVE INGREDIENTS: POVIDONE-IODINE 1 g/100 mL
INACTIVE INGREDIENTS: ALCOHOL; SODIUM HYDROXIDE; WATER; GLYCERIN; MENTHOL

Bernard Jensen PovDine Gargle Solution

Drug Facts

Active ingredient (before dilution)

Povidone-iodine 1%

Purpose

Antiseptic gargle

Use

first aid to help prevent the risk of infection in minor cuts and scrapes caused by dental procedures or accidental injury

Warnings

Do not use for more than 7 days unless directed by a dentist or doctor

Stop use and ask a dentist or doctor if

- sore mouth symptoms do not improve in 7 days
- irritation, pain or redness persists or worsens
- swelling, rash or fever develops

PREGNANCY OR BREAST FEEDING

If pregnant or breast-feeding, ask a health professional before use.

Keep out of reach of children. If more than used for gargling is accidentally swallowed, get medical help or contact a Poison Control Center right away.

Directions

Adults and children 12 years and older:

- dilute 1 tablespoon (15 ml) of product with equal amount of water
- rinse and gargle for 30 seconds, then spit out. Do not swallow solution or rinse mouth afterward
- use up to four times daily for no more than 7 days

Children under 12 years: do not use

Other information

- store at room temperature
- may stain clothing, dentures and braces
- avoid contact with jewelry, especially silver

INACTIVE INGREDIENT

Inactive ingredients. glycerin, menthol, ethyl alcohol (6%), sodium hydroxide, purified water

Questions? (800) 755-4027

Dilute with equal parts water before use.

Sealed with a tamper-evident cap for your protection. If ring band is detached from cap or missing, do not use.

Distributed by:

Bernard Jensen Products

Chula Vista, CA 91911

www.bernardj.com

Made in Mexico

PACKAGE LABEL

Bernard Jensen's

PovDine™

GARGLE SOLUTION

ORAL ANTISEPTIC

1% Povidone-Iodine Concentrated Solution

Mint Flavor

1 fl oz (30 ml)